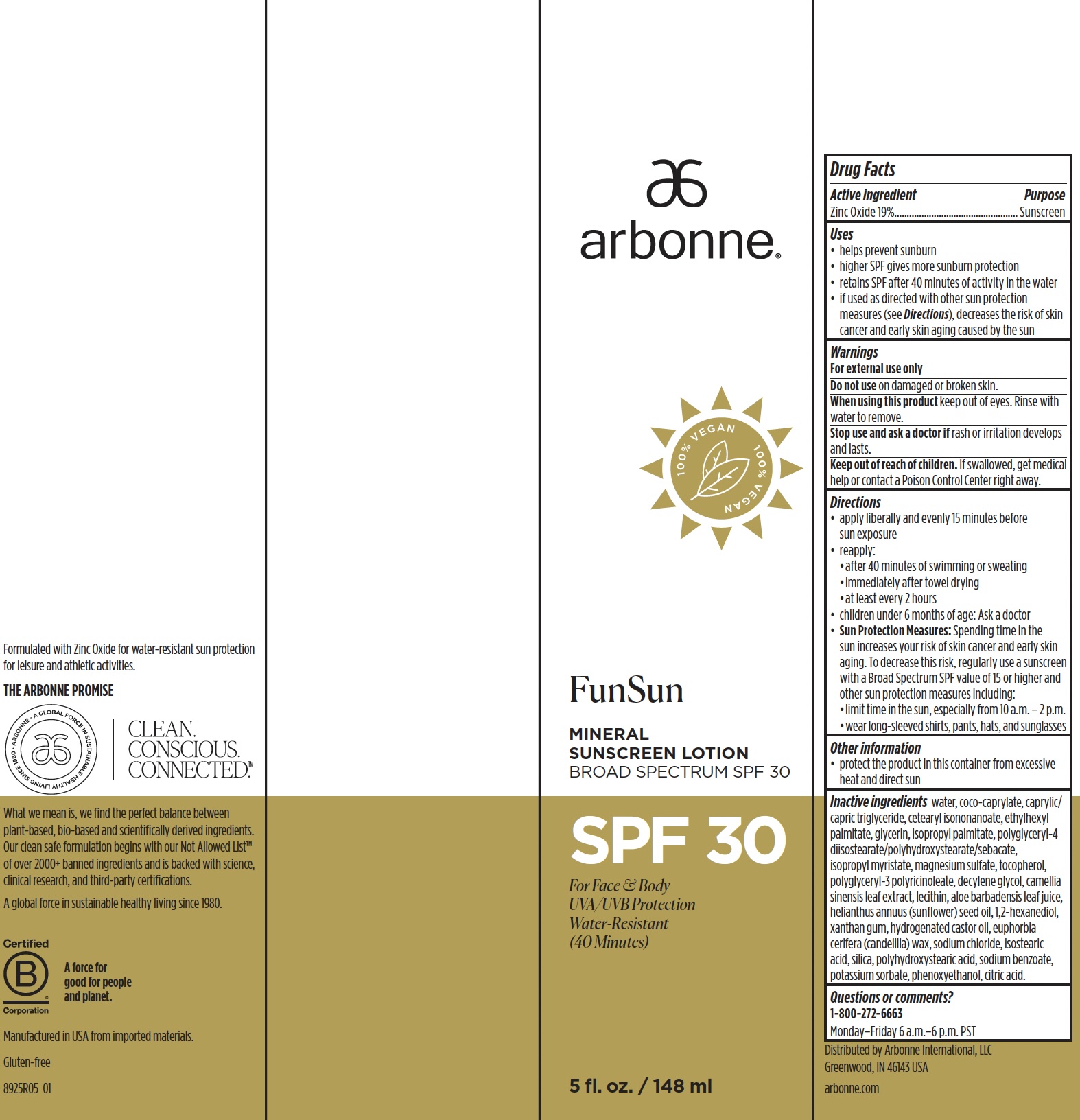 DRUG LABEL: Arbonne FunSun Mineral Sunscreen Broad Spectrum SPF 30
NDC: 42508-805 | Form: LOTION
Manufacturer: Arbonne International, LLC
Category: otc | Type: HUMAN OTC DRUG LABEL
Date: 20251209

ACTIVE INGREDIENTS: ZINC OXIDE 190 mg/1 mL
INACTIVE INGREDIENTS: WATER; COCO-CAPRYLATE; MEDIUM-CHAIN TRIGLYCERIDES; CETEARYL ISONONANOATE; ETHYLHEXYL PALMITATE; GLYCERIN; ISOPROPYL PALMITATE; POLYGLYCERYL-4 DIISOSTEARATE/POLYHYDROXYSTEARATE/SEBACATE; MAGNESIUM SULFATE HEPTAHYDRATE; TOCOPHEROL; POLYGLYCERYL-3 RICINOLEATE; DECYLENE GLYCOL; GREEN TEA LEAF; LECITHIN, SUNFLOWER; ALOE VERA LEAF; SUNFLOWER OIL; 1,2-HEXANEDIOL; XANTHAN GUM; HYDROGENATED CASTOR OIL; CANDELILLA WAX; SODIUM CHLORIDE; ISOSTEARIC ACID; SILICON DIOXIDE; POLYHYDROXYSTEARIC ACID (2300 MW); SODIUM BENZOATE; POTASSIUM SORBATE; PHENOXYETHANOL; ANHYDROUS CITRIC ACID

Arbonne®FunSun Mineral Sunscreen Broad Spectrum SPF 30

Drug Facts

Active ingredient

Zinc Oxide 19%

Purpose

Sunscreen

Uses

- helps prevent sunburn
- higher SPF gives more sunburn protection
- retains SPF after 40 minutes of activity in the water
- if used as directed with other sun protection measures (see Directions), decreases the risk of skin cancer and early skin aging caused by the sun

Warnings

For external use only

Do not useon damaged or broken skin.

WHEN USING

When using this productkeep out of eyes. Rinse with water to remove.

Stop use and ask a doctor ifrash or irritation develops and lasts.

Keep out of reach of children.If swallowed, get medical help or contact a Poison Control Center right away.

Directions

- apply liberally and evenly 15 minutes before sun exposure
- reapply:
  - after 40 minutes of swimming or sweating
  - immediately after towel drying
  - at least every 2 hours
- children under 6 months of age: Ask a doctor
- Sun Protection Measures:Spending time in the sun increases your risk of skin cancer and early skin aging. To decrease this risk, regularly use a sunscreen with a Broad Spectrum SPF value of 15 or higher and other sun protection measures including:
  - limit time in the sun, especially from 10 a.m. – 2 p.m.
  - wear long-sleeved shirts, pants, hats, and sunglasses

Other information

- protect the product in this container from excessive heat and direct sun

Inactive ingredients

water, coco-caprylate, caprylic/capric triglyceride, cetearyl isononanoate, ethylhexyl palmitate, glycerin, isopropyl palmitate, polyglyceryl-4 diisostearate/polyhydroxystearate/sebacate, isopropyl myristate, magnesium sulfate, tocopherol, polyglyceryl-3 polyricinoleate, decylene glycol, camellia sinensis leaf extract, lecithin, aloe barbadensis leaf juice, helianthus annuus (sunflower) seed oil, 1,2-hexanediol, xanthan gum, hydrogenated castor oil, euphorbia cerifera (candelilla) wax, sodium chloride, isostearic acid, silica, polyhydroxystearic acid, sodium benzoate, potassium sorbate, phenoxyethanol, citric acid.

Questions or comments?

1-800-272-6663

Monday–Friday 6 a.m.–6 p.m. PST

Distributed by Arbonne International, LLC
9400 Jeronimo Road, Irvine, CA 92618 USA

PRINCIPAL DISPLAY PANEL - 148 ml Tube Carton

arbonne®

100% VEGAN

FunSun

MINERAL
SUNSCREEN LOTION
BROAD SPECTRUM SPF 30

SPF 30

For Face & Body
UVA/UVB Protection
Water-Resistant
(40 Minutes)

5 fl. oz. / 148 ml